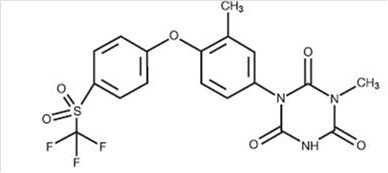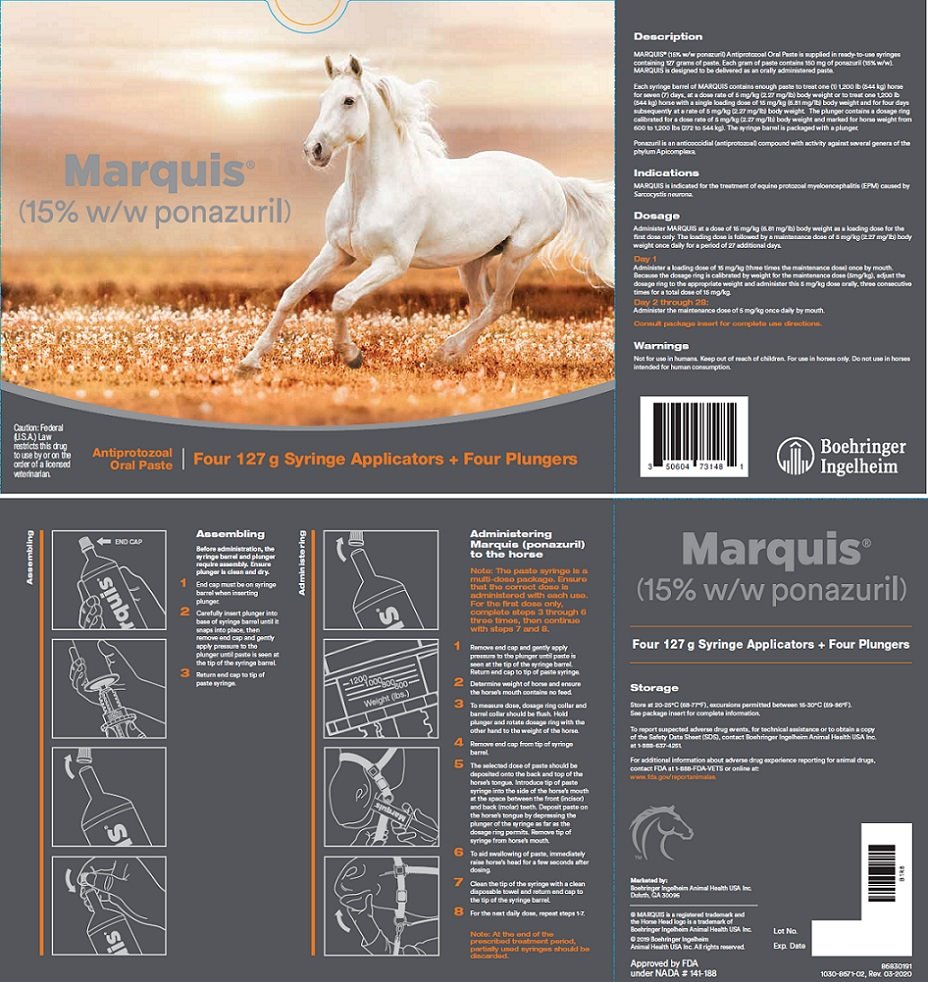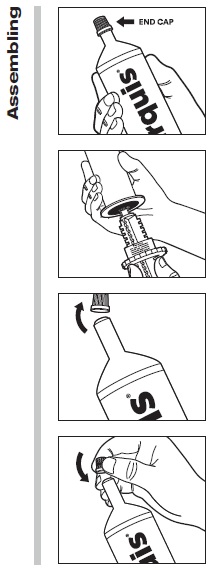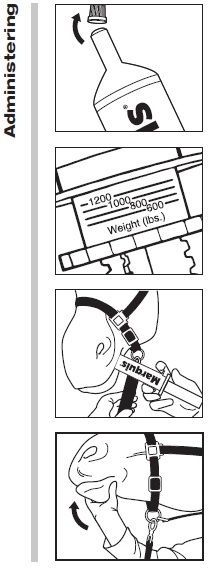 DRUG LABEL: Marquis
NDC: 0010-7314 | Form: PASTE
Manufacturer: Boehringer Ingelheim Animal Health USA Inc.
Category: animal | Type: PRESCRIPTION ANIMAL DRUG LABEL
Date: 20250501

ACTIVE INGREDIENTS: ponazuril 150 mg/1 g

Marquis®
(15% w/w ponazuril)
Antiprotozoal Oral Paste

Caution: Federal (U.S.A.) law restricts this drug to use by or on the order of a licensed veterinarian.

For The Treatment Of Equine Protozoal Myeloencephalitis (EPM) In Horses

For Oral Use Only

Description:

MARQUIS® (15% w/w ponazuril) Antiprotozoal Oral Paste is supplied in a ready-to-use syringe containing 127 grams of paste. Each gram of paste contains 150 mg of ponazuril (15% w/w). MARQUIS is designed to be delivered as an orally administered paste.

Each syringe barrel of MARQUIS contains enough paste to treat one (1) 1,200 lb (544 kg) horse for seven (7) days, at a dose rate of 5 mg/kg (2.27 mg/lb) body weight or to treat one 1,200 lb (544 kg) horse with a single loading dose of 15 mg/kg (6.81 mg/lb) body weight and for four days subsequently at a rate of 5 mg/kg (2.27 mg/lb) body weight. The plunger contains a dosage ring calibrated for a dose rate of 5 mg/kg (2.27 mg/lb) body weight and marked for horse weight from 600 to 1,200 lbs (272 to 544 kg). The syringe barrel is packaged with a plunger. The syringe barrels are packaged in units of four with four reusable plungers and in single syringe units with one reusable plunger.

Ponazuril is an anticoccidial (antiprotozoal) compound with activity against several genera of the phylum Apicomplexa.

Chemical nomenclature and structure: Ponazuril 1,3,5-Triazine-2,4,6(1H,3H,5H)-trione,1-methyl-3-[3-methyl-4-[4-[(trifluoromethyl)sulfonyl] phenoxy]phenyl]-(9Cl)

Clinical pharmacology:

The activity of ponazuril has been demonstrated in several Apicomplexans^1-6. Lindsay, Dubey and Kennedy^7 showed that the concentration of ponazuril necessary to kill Sarcocystis neurona in vitro was 0.1 to 1.0 μg/mL. Furr and Kennedy^8 evaluated the pharmacokinetics of ponazuril in serum and CSF in normal horses treated daily at 5 mg/kg for 28 days. The time to peak serum concentration (Tmax) was 18.20 (±5.9) days and the maximum serum concentration (Cmax) was 5.59 (±0.92) μg/mL. The terminal elimination half-life for serum (calculated using Day 28 to 42 data) was 4.50 (±0.57) days. In CSF, Tmax was 15.40 (±7.9) days and Cmax was 0.21 (±0.072) μg/mL.

A pharmacokinetic study was conducted in eight horses to collect serum and cerebrospinal fluid (CSF) levels of ponazuril after a single dose of 5 mg/kg body weight. The estimated parameter values were used to model time concentration profiles for ponazuril in serum and CSF. The model results were used to estimate the size of the loading dose needed to support the achievement of steady state serum and CSF levels after the first dose. The appropriate loading dose, calculated on the basis of the accumulation ratio (i.e., the fold increase in serum drug concentrations once steady state conditions have been achieved) was 15 mg/kg (6.81 mg/lb) body weight. This dose represents the range of estimated accumulation ratios of 2.3 to 3.3. Thus, a three-fold loading dose (3*5 mg/kg) was selected, leading to achievement of steady state blood levels in horses after one or two days of ponazuril administration.

Indications:

MARQUIS is indicated for the treatment of equine protozoal myeloencephalitis (EPM) caused by Sarcocystis neurona.

Effectiveness Summary:

A field study was conducted at six sites with seven investigators across the United States.^9 The study was conducted using historical controls. In this study, each animal's response to treatment was compared to its pre-treatment values. The following standardized neurologic scale was used to grade the horses:

0 Normal, no deficit detected
1 Deficit just detected at normal gait
2 Deficit easily detected and is exaggerated by backing, turning, swaying, loin pressure or neck extension
3 Deficit very prominent on walking, turning, loin pressure or neck extension
4 Stumbling, tripping and falling down spontaneously
5 Recumbent, unable to rise

Improvement was defined as a decrease of at least one grade.

Naturally-occurring clinical cases of EPM, characterized by signalment and laboratory diagnosis, were randomly allotted to one of two treatment doses (5 or 10 mg/kg/day for a period of 28 days), then evaluated for clinical changes through 118 days. Acceptance into the study was based on the results from a standardized neurological examination including radiography, serum S. neurona IgG level determination by Western Blot (WB), and a positive cerebrospinal fluid (CSF) for S. neurona IgG level by WB.

Response to treatment was determined by the investigator to be acceptable when a clinical improvement of at least one grade occurred by no later than 3 months after treatment, regardless of whether the CSF by WB was positive or negative.

Changes in clinical condition were evaluated first by the subjective scoring of the investigator, then by masked assessment of videotapes of the neurological examination. At 5 mg/kg for 28 days, 28 of 47 horses (60%) improved at least one grade by Day 118. Seventy-five percent (75%) of those improved, that had also been videotaped, were corroborated successes by videotape assessment. At 10 mg/kg, 32 of 55 animals (58%) improved at least one grade by Day 118 and 56% of those improved, that had also been videotaped, were corroborated successes using videotape assessment. With respect to the clinical investigators' scores there was no statistical difference between 5 mg/kg and 10 mg/kg treatment group results (p = 0.8867).

Warnings:

Not for use in humans. Keep out of reach of children. For use in horses only. Do not use in horses intended for human consumption.

Precautions:

Prior to treatment, EPM should be distinguished from other diseases that may cause ataxia in horses. Injuries or lameness may also complicate the evaluation of an animal with EPM. In most instances, ataxia due to EPM is asymmetrical and affects the hind limbs.

Neurologic deficits, primarily ataxia, have been reported to acutely worsen during the early treatment period. In some horses the worsening of the neurologic deficits was transient. (See Post Approval Experience Section).

Clinicians should recognize that clearance of the parasite by ponazuril may not completely resolve the clinical signs attributed to the natural progression of the disease. The prognosis for animals treated for EPM may be dependent upon the severity of disease and the duration of the infection prior to treatment.

The safe use of MARQUIS in horses used for breeding purposes, during pregnancy, or in lactating mares, has not been evaluated. The safety of MARQUIS with concomitant therapies in horses has not been evaluated.

Adverse Reactions:

In the field study, eight animals were noted to have unusual daily observations. Two horses exhibited blisters on the nose and mouth at some point in the field study, three animals showed a skin rash or hives for up to 18 days, one animal had loose stools throughout the treatment period, one had a mild colic on one day and one animal had a seizure while on medication. The association of these reactions to treatment was not established.

Post Approval Experience (2015):

The following adverse events in horses are based on post-approval adverse drug experience reporting. Not all adverse events are reported to FDA/CVM. It is not always possible to reliably estimate the adverse event frequency or establish a causal relationship to product exposure using these data. The following adverse events have been reported:

Neurologic deficits, primarily ataxia, have been reported to acutely worsen during the early treatment period. Although outcome was not always reported, in some horses the worsening of the neurologic deficits was transient.

To report suspected adverse drug events, for technical assistance or to obtain a copy of the Safety Data Sheet (SDS), contact Boehringer Ingelheim Animal Health USA Inc. at 1-888-637-4251.

For additional information about adverse drug experience reporting for animal drugs, contact FDA at 1-888-FDA-VETS or online at www.fda.gov/reportanimalae.

Animal Safety Summary:

MARQUIS was administered to 24 adult horses (12 males and 12 females) in a target animal safety study. Three groups of 8 horses each received 0, 10, or 30 mg/kg (water as control, 2X and 6X for a 5 mg/kg [2.27 mg/lb] dose). Horses were dosed after feeding. One half of each group was treated for 28 days and the other half for 56 days followed by necropsy upon termination of treatment. There were several instances of loose feces in all animals in the study irrespective of treatment, sporadic inappetence and one horse at 10 mg/kg (2X) lost weight while on test. Loose feces were treatment related. Histopathological findings included moderate edema in the uterine epithelium of three of the four females in the 6X group (two treated for 28 days and one for 56 days).

Dosage:

Administer MARQUIS at a dose of 15 mg/kg (6.81 mg/lb) body weight as a loading dose for the first dose only. The loading dose is followed by a maintenance dose of 5 mg/kg (2.27 mg/lb) body weight once daily for a period of 27 additional days.

Day 1: Administer a loading dose of 15 mg/kg (three times the maintenance dose) once by mouth. Because the dosage ring is calibrated by weight for the maintenance dose (5mg/kg), adjust the dosage ring to the appropriate weight and administer this 5 mg/kg dose orally, three consecutive times for a total dose of 15 mg/kg.

Day 2 through 28: Administer the maintenance dose of 5 mg/kg once daily by mouth.

Assembling

Before administration, the syringe barrel and plunger require assembly. Ensure plunger is clean and dry.

1. End cap must be on syringe barrel when inserting plunger.
2. Carefully insert plunger into base of syringe barrel until it snaps into place, then remove end cap and gently apply pressure to the plunger until paste is seen at the tip of the syringe barrel.
3. Return end cap to tip of paste syringe.

Administering MARQUIS to the horse:

Note: The paste syringe is a multi-dose package. Ensure that the correct dose is administered with each use. For the first dose only, complete steps 3 through 6 three times, then continue with steps 7 and 8.

1. Remove end cap and gently apply pressure to the plunger until paste is seen at the tip of the syringe barrel. Return end cap to tip of paste syringe.
2. Determine weight of horse and ensure the horse's mouth contains no feed.
3. To measure dose, dosage ring collar and barrel collar should be flush. Hold plunger and rotate dosage ring with the other hand to the weight of the horse.
4. Remove end cap from tip of syringe barrel.
5. The selected dose of paste should be deposited onto the back and top of the horse's tongue. Introduce tip of paste syringe into the side of the horse's mouth at the space between the front (incisor) and back (molar) teeth. Deposit paste on the horse's tongue by depressing the plunger of the syringe as far as the dose ring permits. Remove tip of syringe from horse's mouth.
6. To aid swallowing of paste, immediately raise horse's head for a few seconds after dosing.
7. Clean the tip of the syringe with a clean disposable towel and return end cap to tip of syringe barrel.
8. For the next daily dose, repeat steps 1-7.

Note:At the end of the prescribed treatment period, partially used syringes should be discarded.

Storage:

Store at 20-25°C (68-77°F), excursions permitted between 15-30°C (59-86°F).

How Supplied:

Code: 86830183 Carton contains one (1) X 127 gram syringe applicator and one (1) syringe plunger.

Code: 86830191 Carton contains four (4) X 127 gram syringe applicators and four (4) syringe plungers.

Marketed by: Boehringer Ingelheim Animal Health USA Inc.

Duluth, GA 30096

Approved by FDA under NADA #141-188

© 2019 Boehringer Ingelheim Animal Health USA Inc.

All rights reserved.
® MARQUIS is a registered trademark and the Horse Head logo is a trademark of Boehringer Ingelheim Animal Health USA Inc.

86830175
1050-8672-02
03/2020

References:

1. Mehlhorn, H., Ortmann-Falkenstein, G., Haberkorn, A.: (1984) The effects of the sym. Trianzinons on developmental stages of Eimeria tenella, E. maxima and E. acervulina: a light and electron microscopical study. Zeitschr Parsitenk 70: 173-182.
2. Bohrmann, R.: (1991) Treatment with toltrazuril in a natural outbreak of coccidiosis in calves. Dtsch. Tierarzl. Wschr. 98: 343-345.
3. Stafford, K.J., West, D.M., Vermunt, J.J., Pomroy, W., Adlington, B.A., Calder, S.M.: (1994) The effect of repeated doses of toltrazuril on coccidial oocyst output and weight gain in infected lambs. NZ Vet J 42(3): 117-119.
4. Haberkorn, A.G., Stoltefuss, D.I.J.: (1987) Studies on the activity spectrum of toltrazuril, a new anti-coccidial compound. Vet. Med. Review 1: 22-32.
5. Koudela, B., Vodstricilova, M., Klimes, B., Vladik, P., Vitovec, J.: (1991) Application of the anticoccidiosis drug Toltrazuril in the coccidiosis of neonatal pigs. Veterinami medicina (Praha) 36: 657-663.
6. Benoit, E., Buronfosse, T., Delatour, P.: (1994) Effect of Cytochrome P-450 1A induction on enantioselective metabolism and pharmacokinetics of an aryltrifluoromethyl sulfide in the rat. Chirality 6(5): 372-377.
7. Lindsay, D.S., Dubey, J.P., Kennedy, T.J.: (2000) Determination of the activity of ponazuril against Sarcocystis neurona in cell cultures. Vet Parasit 92: 165-169.
8. Furr, M., Kennedy, T.: Pharmacokinetics of ponazuril in horses. Study 150-717 Bayer Corporation.
9. Furr, M., Andrews, F., MacKay, R., Reed, S., Bernard, W., Bain, F., Byars, D., Kennedy, T.: Treatment of equine protozoal myeloencephalitis (EPM) with various doses of ponazuril. Study Report 150-664 Bayer Corporation.

PRINCIPAL DISPLAY PANEL – 127 g syringe applicator carton

Marquis®
(15% w/w ponazuril)

Antiprotozoal Oral Paste

Four 127 g Syringe Applicators + Four Plungers

CAUTION: Federal (U.S.A.) Law restricts this drug to use by or on the order of a licensed veterinarian.